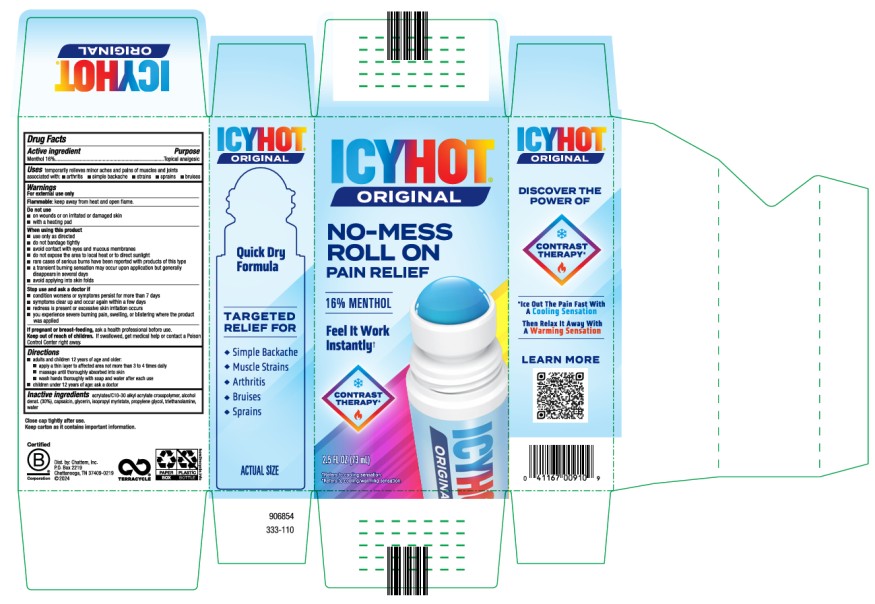 DRUG LABEL: Icy Hot Medicated No Mess Applicator
NDC: 41167-0091 | Form: LIQUID
Manufacturer: Chattem, Inc.
Category: otc | Type: HUMAN OTC DRUG LABEL
Date: 20250201

ACTIVE INGREDIENTS: MENTHOL 0.16 g/1 mL
INACTIVE INGREDIENTS: CARBOMER INTERPOLYMER TYPE A (55000 CPS); ALCOHOL; CAPSAICIN; GLYCERIN; ISOPROPYL MYRISTATE; PROPYLENE GLYCOL; TROLAMINE; WATER

Icy Hot - Medicated No Mess Applicator

Icy Hot® - Medicated No Mess Applicator

Active ingredient

Menthol 16%

Purpose

Topical analgesic

Uses

temporarily relieves minor pain associated with:

- arthritis
- simple backache
- strains
- sprains
- bruises

Warnings

For external use only

Flammable: keep away from heat and open flame.

Do not use

■ on wounds or on irritated or damaged skin

■ with a heating pad

When using this product

■ use only as directed

■ do not bandage tightly

■ avoid contact with eyes and mucous membranes

■ do not expose the area to local heat or to direct sunlight

■ rare cases of serious burns have been reported with products of this type

■ a transient burning sensation may occur upon application but generally disappears in several days

■ avoid applying into skin folds

Stop use and ask a doctor if

■ condition worsens or symptoms persist for more than 7 days

■ symptoms clear up and occur again within a few days

■ redness is present or excessive skin irritation occurs

■ you experience severe burning pain, swelling, or blistering where the product was applied

If pregnant or breast-feeding,

ask a health professional before use.

Keep out of reach of children.

If swallowed, get medical help or contact a Poison Control Center right away.

Directions

■ adults and children 12 years of age and older:

■ apply a thin layer to affected area not more than 3 to 4 times daily

■ massage until thoroughly absorbed into skin

■ wash hands thoroughly with soap and water after each use

■ children under 12 years of age: ask a doctor

Inactive ingredients

acrylates/C10-30 alkyl acrylate crosspolymer, alcohol denat. (30%), capsaicin, glycerin, isopropyl myristate, propylene glycol, triethanolamine, water

Close cap tightly after use.

Principal Display Panel

ICY HOT®

ORIGINAL
NO-MESS
ROLL ON
PAIN RELIEF
16% MENTHOL

2.5 fl oz (73 m L)